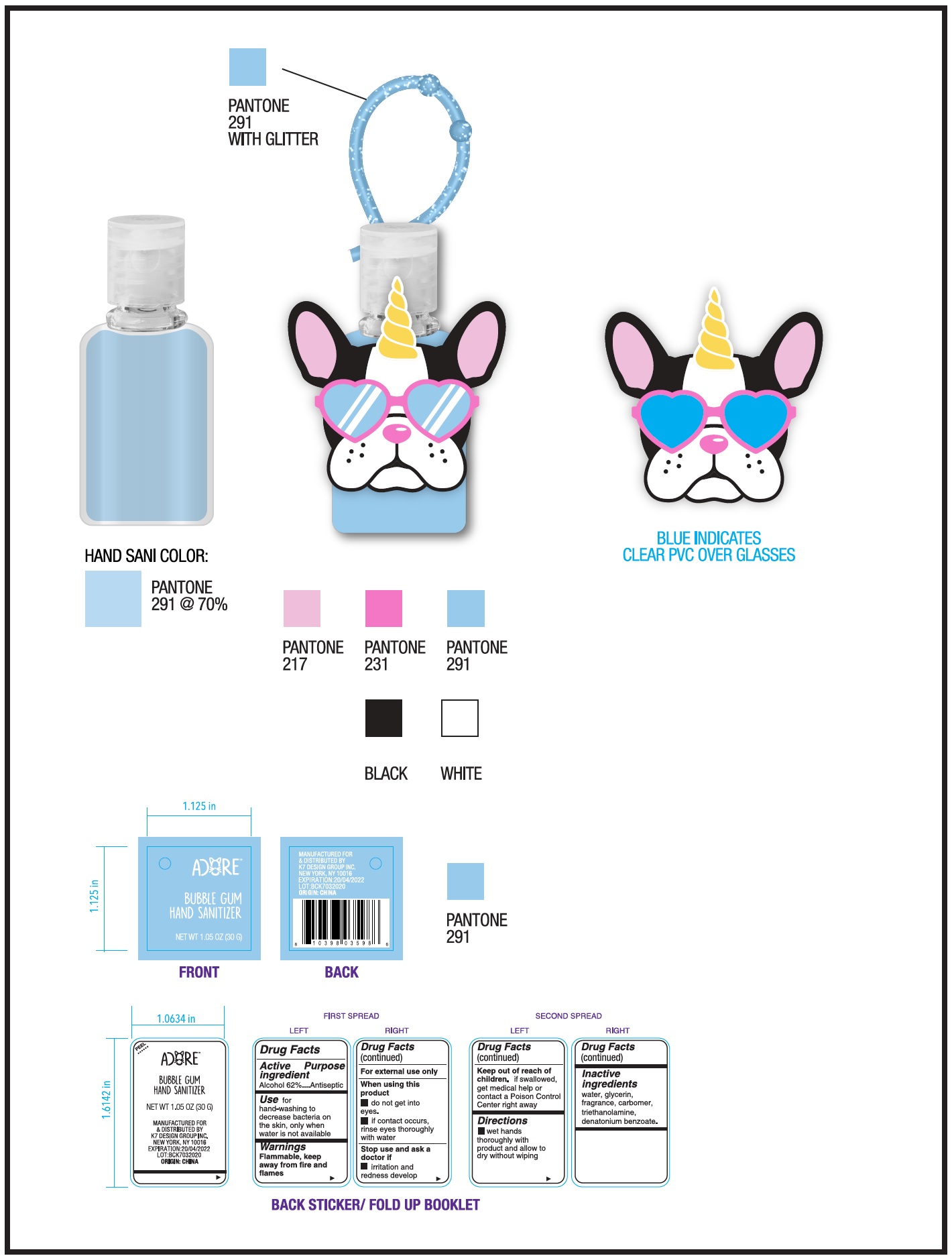 DRUG LABEL: BUBBLE GUM HAND SANITIZER girl
NDC: 74177-023 | Form: GEL
Manufacturer: K7 Design Group Inc.
Category: otc | Type: HUMAN OTC DRUG LABEL
Date: 20231026

ACTIVE INGREDIENTS: ALCOHOL 0.62 g/1 g
INACTIVE INGREDIENTS: WATER; GLYCERIN; CARBOXYPOLYMETHYLENE; TROLAMINE; DENATONIUM BENZOATE

BUBBLE GUM HAND SANITIZER-girl

Active ingredient

Alcohol 62%

Purpose

Antiseptic

Use

for hand-washing to decrease bacteria on the skin, only when water is not available

Warnings

Flammable, keep away from fire or flames

For external use only

When using this product

- do not get into eyes.
- if contact occurs, rinse eyes thoroughly with water

Stop use and ask a doctor if

Irritation and redness develop

Keep out of reach of children.

If swallowed, get medical help or contact a Poison Control Center right away.

Directions

- wet hands thoroughly with product and allow to dry without wiping

Inactive ingredients

water, glycerin, fragrance, carbomer, triethanolamine, denatonium benzoate.